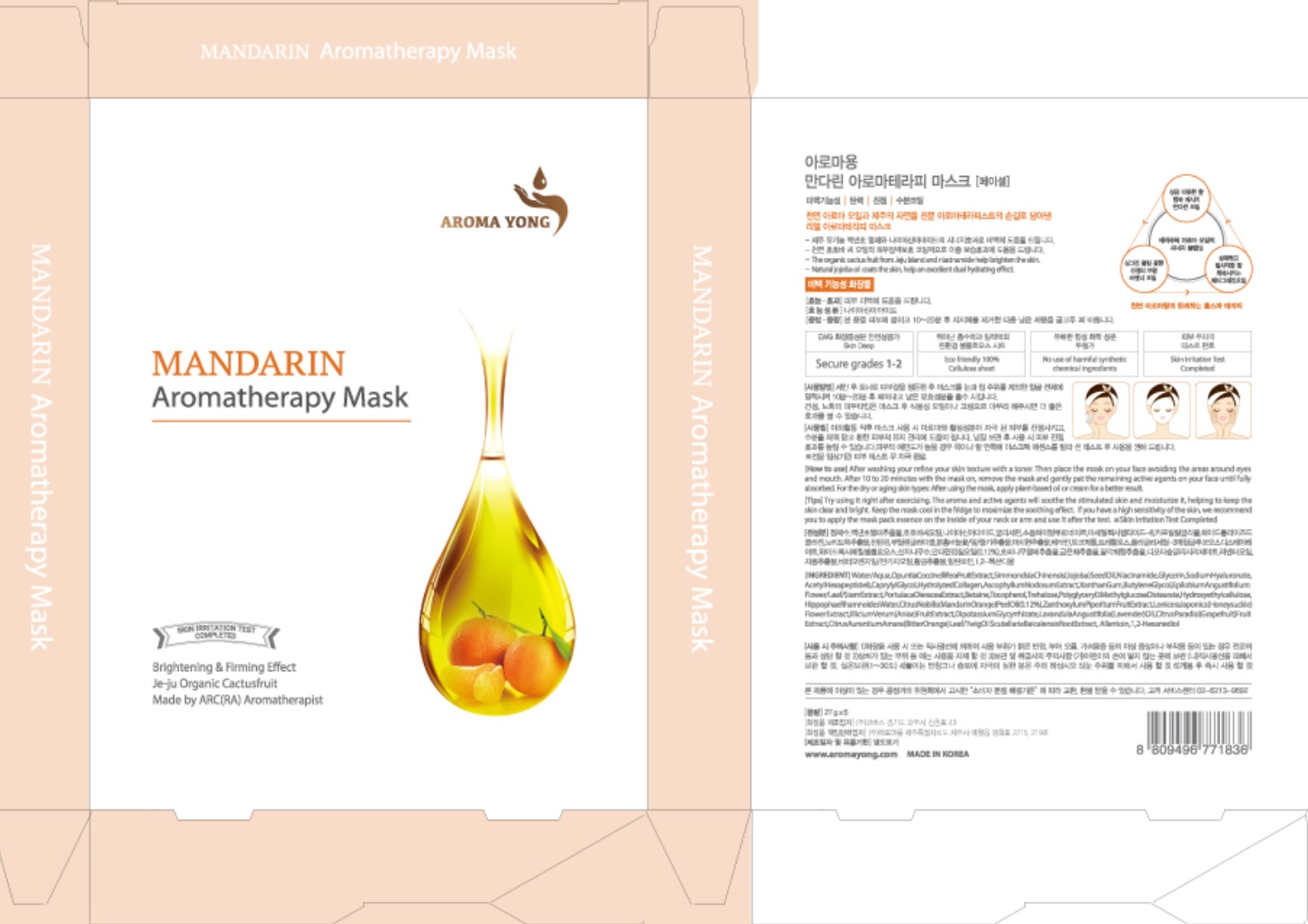 DRUG LABEL: FRESH MANDARIN AROMATHERAPY MASK
NDC: 71392-060 | Form: PATCH
Manufacturer: AROMA YONG
Category: otc | Type: HUMAN OTC DRUG LABEL
Date: 20191203

ACTIVE INGREDIENTS: NIACINAMIDE 0.54 g/27 g
INACTIVE INGREDIENTS: WATER; BUTYLENE GLYCOL

71392-060

ACTIVE INGREDIENT

Active ingredients: Niacinamide2.0%

INACTIVE INGREDIENT

Inactive ingredients:

Aqua/Water, Opuntia Coccinellifera Fruit Extract, Simmondsia Chinensis Seed Oil, Glycerin, Ascophyllum, Nodosum Extract, Hydroxyethylcellulose, Butylene Glycol, Epilobium Angustifolium Flower/Leaf/Stem Extract, Portulaca Oleracea Extract, Citrus Nobilis Peel Oil, Betaine, Tocopherol, Xanthan Gum, Polyglyceryl-3 Methylglucose Distearate, Trehalose, Hippophae Rhamnoides Water, Zanthoxylum Piperitum Fruit Extract, Lonicera Japonica Flower Extract, Illicium Verum Fruit Extract, Lavandula Angustifolia Oil, Dipotassium Glycyrrhizate, Citrus Aurantium Amara Leaf/Twig Oil, Citrus Paradisi Fruit Extract, Scutellaria Baicalensis Root Extract, Allantoin, Sodium Hyaluronate, Disodium Phosphate, Polysorbate 60, Sodium Phosphate, Caprylyl Glycol, Hydrolyzed Collagen, 1,2-Hexanediol, Acetyl Hexapeptide-8, Limonene**, Linalool**, Citral** ** From pure essential oil

PURPOSE

Purpose: Skin Brightening & firming effect

WARNINGS

1) Do not use on damaged or irritated skin and skin with dermatitis 2) Do not use immediately after dermatological treatment or cosmetic surgery .3) Do not use in case of allergy to any of the ingredients 4) For external use only. 5) Do not use directly before exposure to the sunlight 6) Discontinue use if signs of irritation or rashes appear and consult with doctor. 7) Avoid direct contact with eyes. 8) Please be careful if you are irritating to adhesive bandages or patches. 9) Store in a cool and dry place, away from direct sunlight and heath (temperature storage 1-30 degrees), keep out of the reach of children.

KEEP OUT OF REACH OF CHILDREN

Uses

Help increase Brightening in the skin

Jeju Organic Cactusfruit + blended pure essential oil (Made by ARC (RA)Aromatherapist) Skin Irritation Test Completed / Eco friendly100% Cellulose sheet

Directions

After washing your face, refine your skin texture with a toner. Then place the mask on your face avoiding the areas around eyes and mouth. After 10 to 20 minutes with the mask on, remove the mask and gently pat the remaining active agents on your face until fully absorbed.

For the dry or aging skin types: After using the mask, apply plant-based oil or cream for a better result.